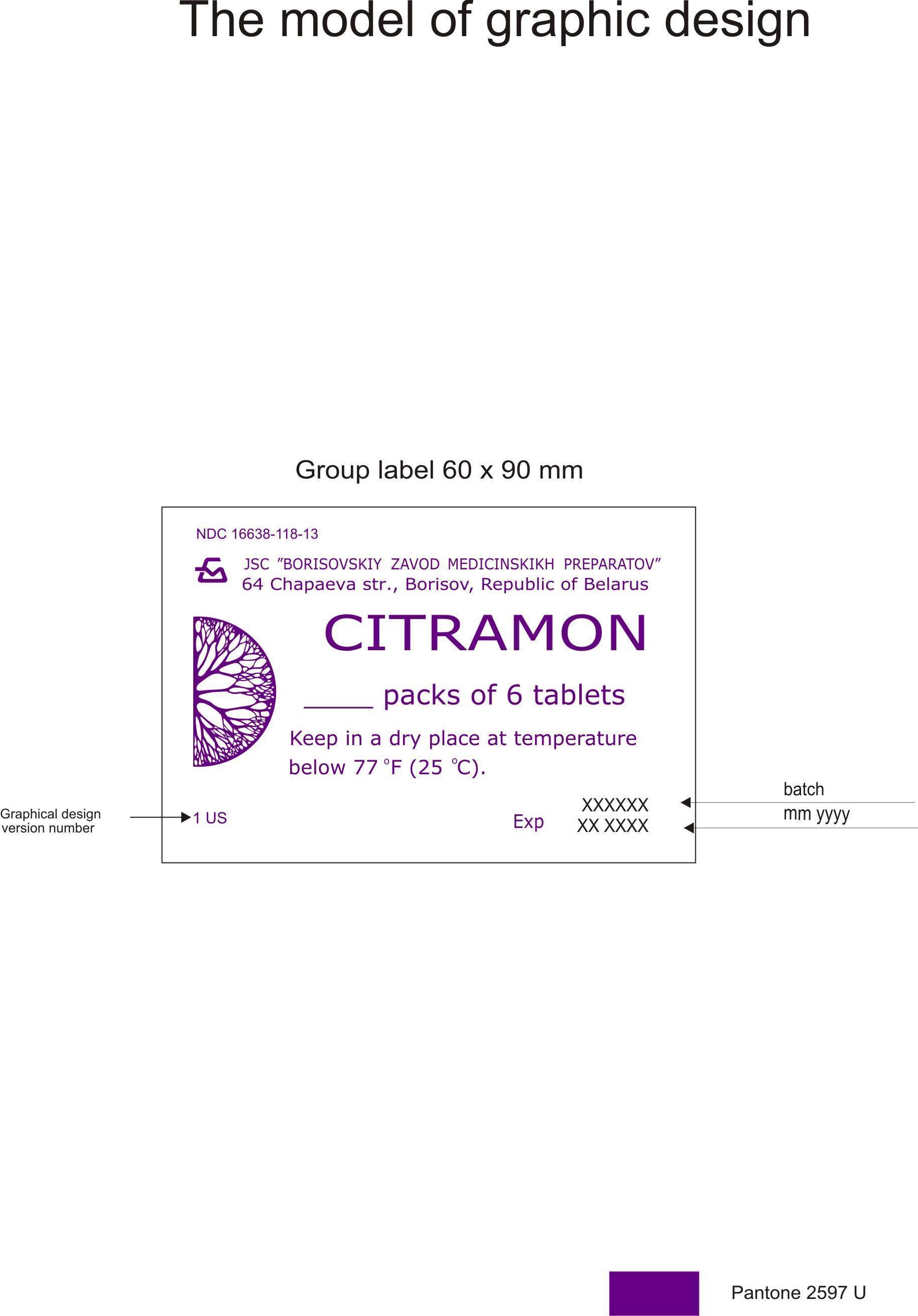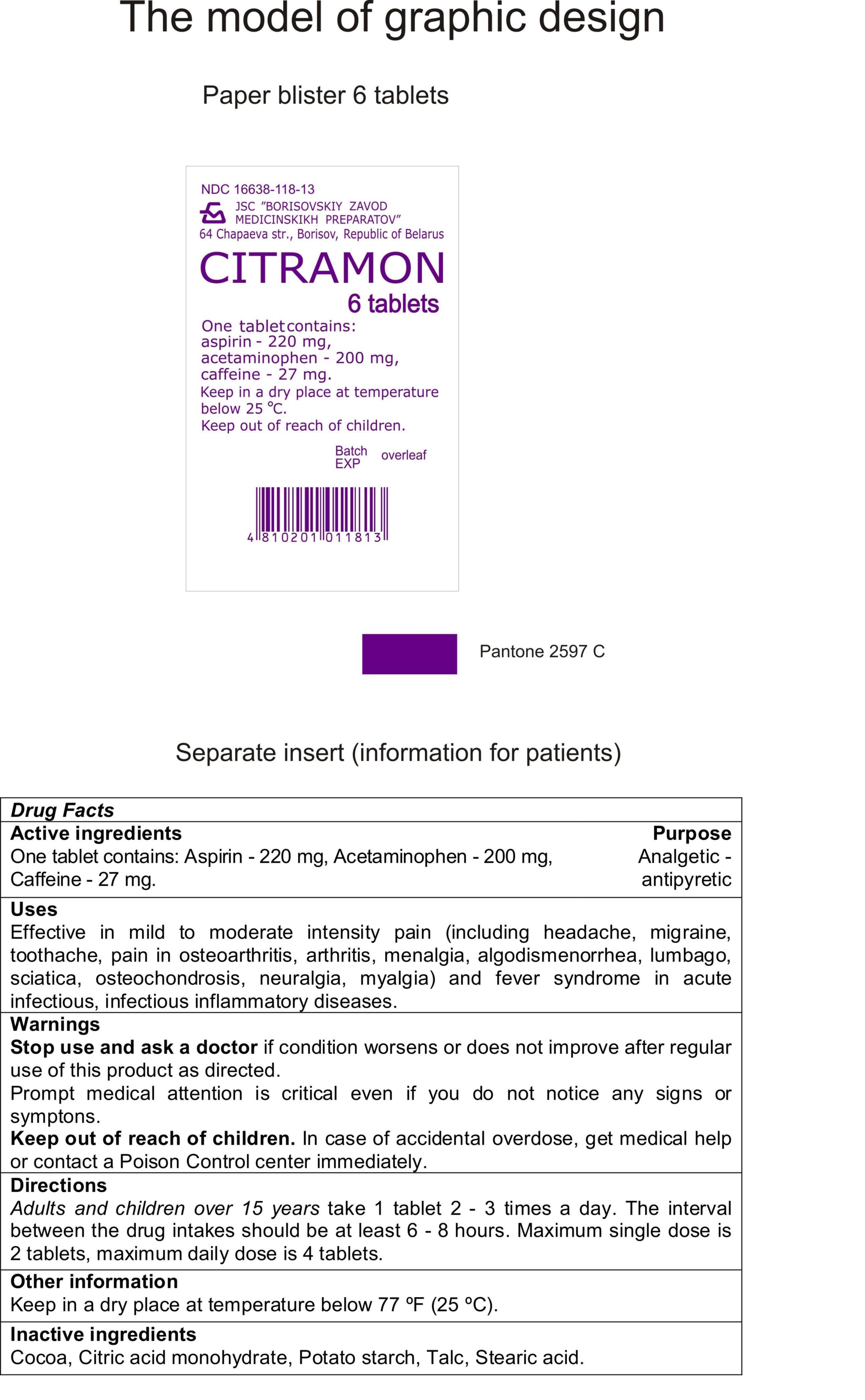 DRUG LABEL: CITRAMON
NDC: 16638-118 | Form: TABLET
Manufacturer: Borisovskiy Zavod Medicinskikh Preparatov JSC
Category: otc | Type: HUMAN OTC DRUG LABEL
Date: 20160824

ACTIVE INGREDIENTS: ASPIRIN 220 mg/550 mg; ACETAMINOPHEN 200 mg/550 mg; CAFFEINE 27 mg/550 mg
INACTIVE INGREDIENTS: COCOA 22.5 mg/550 mg; CITRIC ACID MONOHYDRATE 4.6 mg/550 mg; STARCH, POTATO 68 mg/550 mg; TALC 2.4 mg/550 mg; STEARIC ACID 7.15 mg/550 mg

Drug facts

Active ingredients

One tablet contains: Aspirin - 220 mg, Acetaminophen - 200 mg, Caffeine - 27 mg.

Purpose

Analgetic - antipyretic

Uses

Effective in mild to moderate intensity pain (including headache, migraine, toothache, pain in osteoarthritis, arthritis, menalgia, algodismenorrhea, lumbago, sciatica, osteochondrosis, neuralgia, myalgia) and fever syndrome in acute infectious, infectious inflammatory diseases.

Warnings

Stop use and ask a doctor if condition worsens or does not improve after regular use of this product as directed.

Prompt medical attention is critical even if you do not notice any signs or symptons.

Keep out of reach of children. In case of accidental overdose, get medical help or contact a Poison Control center immediately.

Directions

Adults and children over 15 years take 1 tablet 2 - 3 times a day. The interval between the drug intakes should be at least 6 - 8 hours. Maximum single dose is 2 tablets, maximum daily dose is 4 tablets.

Other information

Keep in a dry place at temperature below 77 ºF (25 ºC).

Inactive ingredients

Cocoa, Citric acid monohydrate, Potato starch, Talc, Stearic acid.